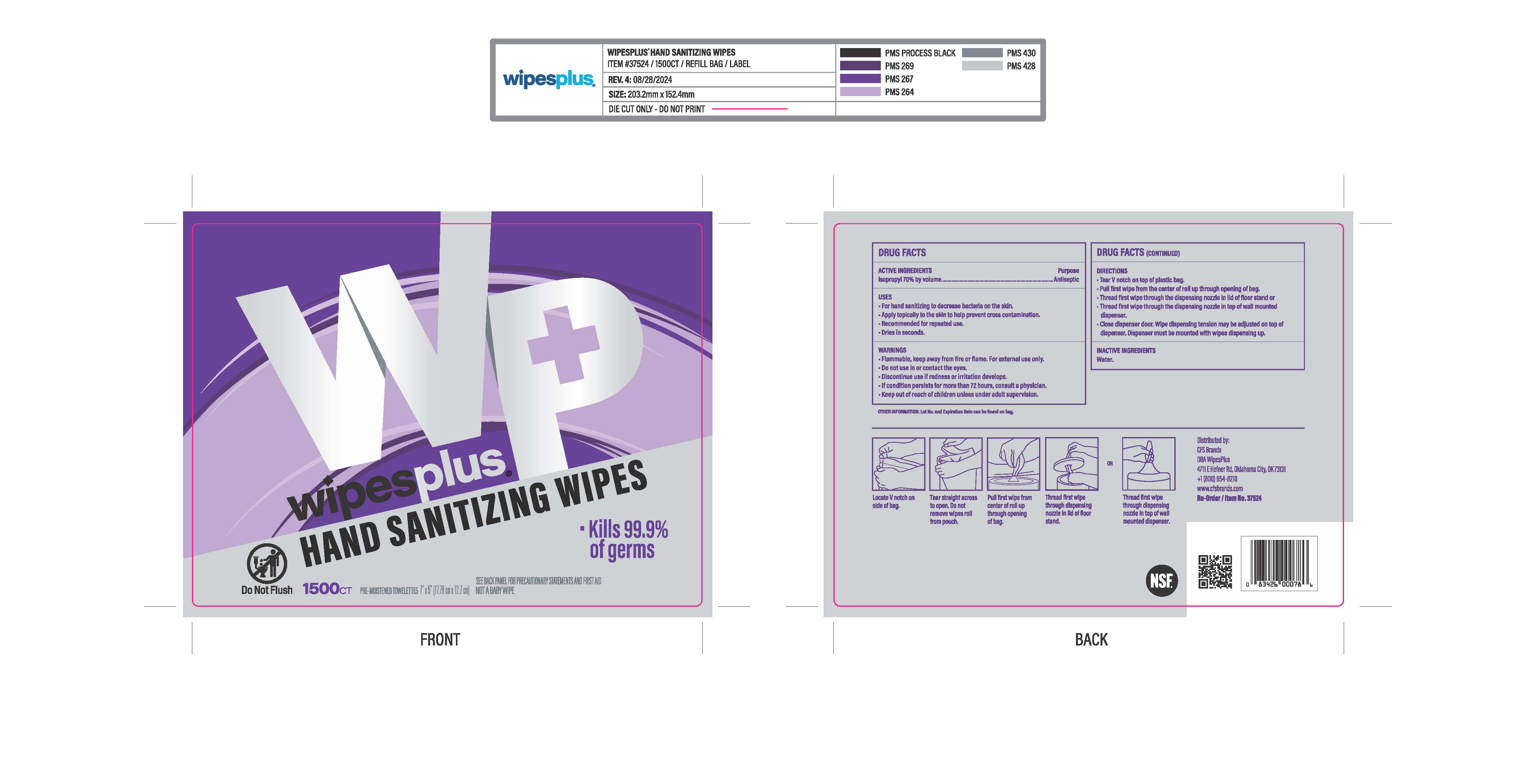 DRUG LABEL: WIPESPLUS HAND SANITIZING WIPES
NDC: 84376-001 | Form: CLOTH
Manufacturer: CFS Brands
Category: otc | Type: HUMAN OTC DRUG LABEL
Date: 20250421

ACTIVE INGREDIENTS: ALCOHOL 4.2 g/1 1
INACTIVE INGREDIENTS: WATER

ALCOHOL, WIPESPLUS HAND SANITIZING WIPES

Active ingredient alcohol 70%

Purpose antiseptic

INDICATIONS AND USAGE

Use For hand sanitizing to decrease bacteria on the skin.

Warnings

for external use only.

Flammable, keep away from flame or heat

Do not use in or contact with eyes

Stop use and ask a doctor • if redness or irritation develops

• If conditions persist for more than 72 hours, consult a physician

Keep out of reach of children unless under adult supervision.

Directions

- rub wipe thoroughly over all surfaces of both hands
- allow to dry without wiping
- supervise children under 6 years old
- not recommended for infants
- dispose of wipe in trash; do not flush

Inactive ingredient: water